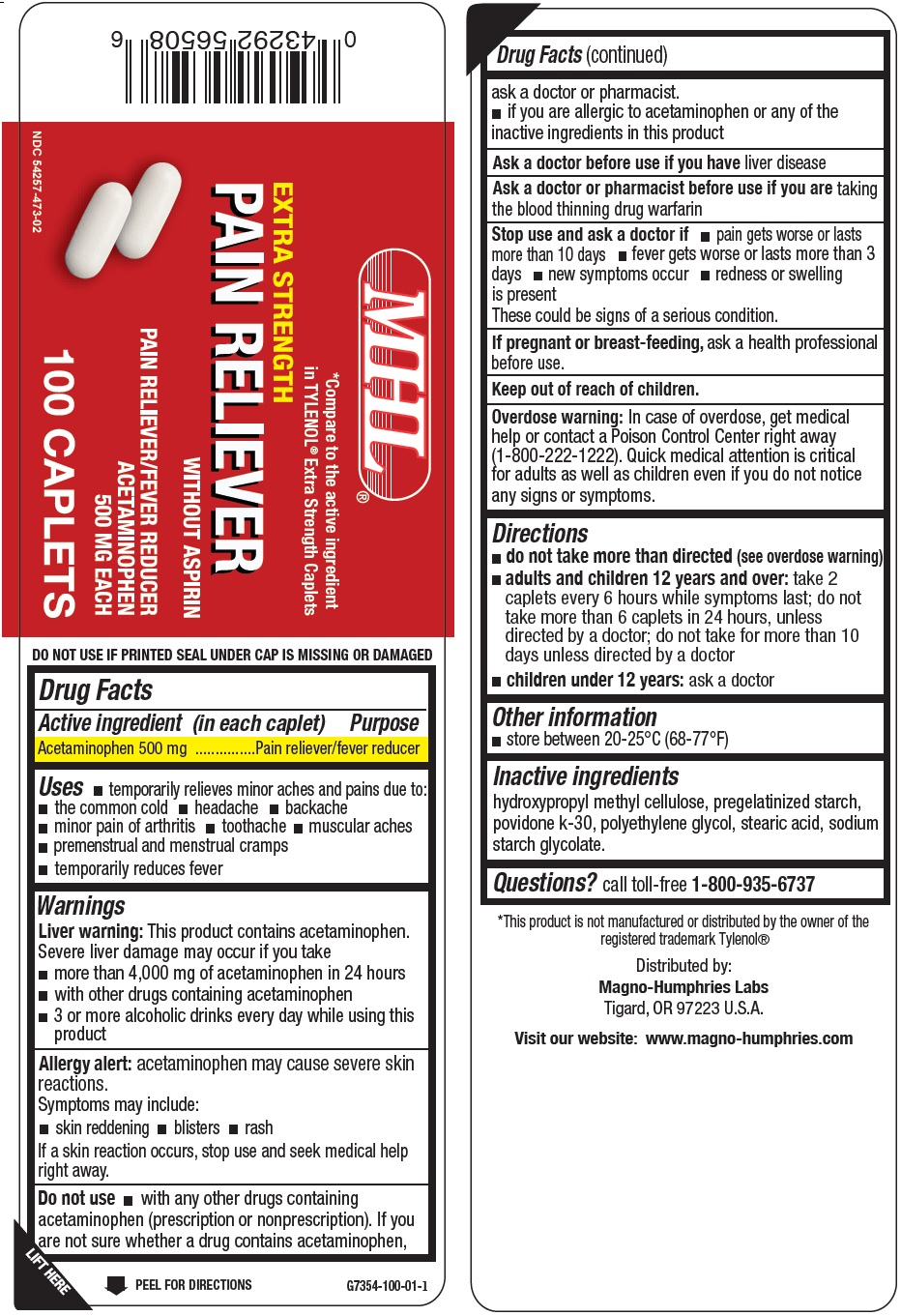 DRUG LABEL: Pain Reliever
NDC: 54257-473 | Form: TABLET
Manufacturer: Magno-Humphries, Inc.
Category: otc | Type: HUMAN OTC DRUG LABEL
Date: 20231027

ACTIVE INGREDIENTS: ACETAMINOPHEN 500 mg/1 1
INACTIVE INGREDIENTS: POLYETHYLENE GLYCOL, UNSPECIFIED; STEARIC ACID

Pain Reliever

Active ingredient (in each caplet)

Acetaminophen 500 mg

Purpose

Pain reliever/fever reducer

Uses

- temporarily relieves minor aches and pains due to:
- the common cold
- headache
- backache
- minor pain of arthritis
- toothache
- muscular aches
- premenstrual and menstrual cramps
- temporarily reduces fever

Warnings

This product contains acetaminophen. Severe liver damage may occur if you take Liver warning:

acetaminophen may cause severe skin reactions. Allergy alert:

Symptoms may include:

If a skin reaction occurs, stop use and seek medical help right away.

- more than 4,000 mg of acetaminophen in 24 hours
- with other drugs containing acetaminophen
- 3 or more alcoholic drinks every day while using this product

- skin reddening
- blisters
- rash

Do not use

- with any other drugs containing acetaminophen (prescription or nonprescription). If you are not sure whether a drug contains acetaminophen, ask a doctor or pharmacist.
- if you are allergic to acetaminophen or any of the inactive ingredients in this product

Ask a doctor before use if you have

liver disease

Ask a doctor or pharmacist before use if you are

taking the blood thinning drug warfarin

Stop use and ask a doctor if

- pain gets worse or lasts more than 10 days
- fever gets worse or lasts more than 3 days
- new symptoms occur
- redness or swelling is present

These could be signs of a serious condition.

If pregnant or breast-feeding,

ask a health professional before use.

Keep out of reach of children.

In case of overdose, get medical help or contact a Poison Control Center right away (1-800-222-1222). Quick medical attention is critical for adults as well as children even if you do not notice any signs or symptoms. Overdose warning:

Directions

- (see overdose warning) do not take more than directed
- take 2 caplets every 6 hours while symptoms last; do not take more than 6 caplets in 24 hours, unless directed by a doctor; do not take for more than 10 days unless directed by a doctor adults and children 12 years and over:
- ask a doctor children under 12 years:

Other information

- store between 20º to 25ºC (68º to 77º F)

Inactive ingredients

hydroxypropyl methyl cellulose, pregelatinized starch, povidone k-30, polyethylene glycol, stearic acid, sodium starch glycolate.

Questions?

call toll-free 1-800-935-6737